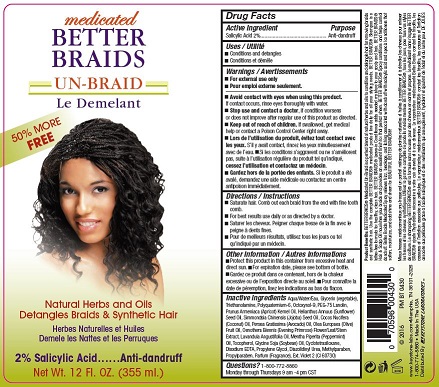 DRUG LABEL: Better Braids Medicated Un-Braid
NDC: 58318-004 | Form: SPRAY
Manufacturer: Keystone Laboratories
Category: otc | Type: HUMAN OTC DRUG LABEL
Date: 20160929

ACTIVE INGREDIENTS: SALICYLIC ACID 2 mg/355 mL
INACTIVE INGREDIENTS: WATER; TRIETHANOLAMINE TRIS(DIHYDROGEN PHOSPHATE); PROPYLENE GLYCOL; PRUNUS AMERICANA WHOLE; APRICOT KERNEL OIL; DIAZOLIDINYL UREA; SIMMONDSIA CHINENSIS LEAF; EDETATE DISODIUM; LAVANDULA ANGUSTIFOLIA FLOWER; MENTHA PIPERITA LEAF; FD&C YELLOW NO. 5; .ALPHA.-TOCOPHEROL ACETATE; METHYLPARABEN; PROPYLPARABEN; GLYCINE; 2,4,6,8-TETRAMETHYL-2,4,6,8-TETRAVINYLCYCLOTETRASILOXANE; GLYCERIN; PEG-75 LANOLIN; HELIANTHUS ANNUUS FLOWERING TOP; COCOS NUCIFERA WHOLE; AVOCADO OIL; OLEA EUROPAEA FLOWER; OENOTHERA BIENNIS FLOWERING TOP; EXT. D&C VIOLET NO. 2; POLYQUATERNIUM-6 (15000 MW); OCTOXYNOL-9

Active Ingredient: Salicylic Acid

PURPOSE

Anti - dandruff

Keep out of reach of children

Directions

Spray generously on hair and massage into scalp.
Style as usual.
For best results use daily or as directed by a doctor.

Vaporisez généreusement sur les cheveux et massez le cuir
chevelu. Coiffez comme à l’habitude.
Pour de meilleurs résultats, utilisez tous les jours ou tel
qu’indiqué par un médecin.

WARNINGS

For external use only

Avoid contact with eyes when using this product.
If contact occurs, rinse eyes thoroughly with water.
Stop use and contact a doctor, if condition worsens
or does not improve after regular use of this product as directed.
Keep out of reach of children. If swallowed, get medical
help or contact a Poison Control Center right away.

Lors de l’utilisation du produit, évitez tout contact avec
les yeux. S’il y avait contact, rincez les yeux minutieusement
avec de l’eau. Si les conditions s’aggravent ou ne s’améliorent
pas, suite à l’utilisation régulière du produit tel qu’indiqué,
cessez l’utilisation et contactez un médecin.
Gardez hors de la portée des enfants. Si le produit a été
avalé, demandez une aide médicale ou contactez un centre
antipoison immédiatement.

Inactive ingredients

Aqua/Water/Eau, Glycerin (vegetable),
Triethanolamine, Octoxynol-9, Polyquaternium-6, Propylene Glycol,
Diazolidinyl Urea, Methylparaben, Propylparaben, Disodium EDTA,
Cyclotetrasiloxane, Parfum (Fragrance)

Other Information / Autres informations
Protect this product in this container from excessive heat and
direct sun. For expiration date, please see bottom of bottle.

Usage
Reduce frizz, breakage and itching

Utilitè
Réduit les frisottis, les cassures et les demangéaisons.